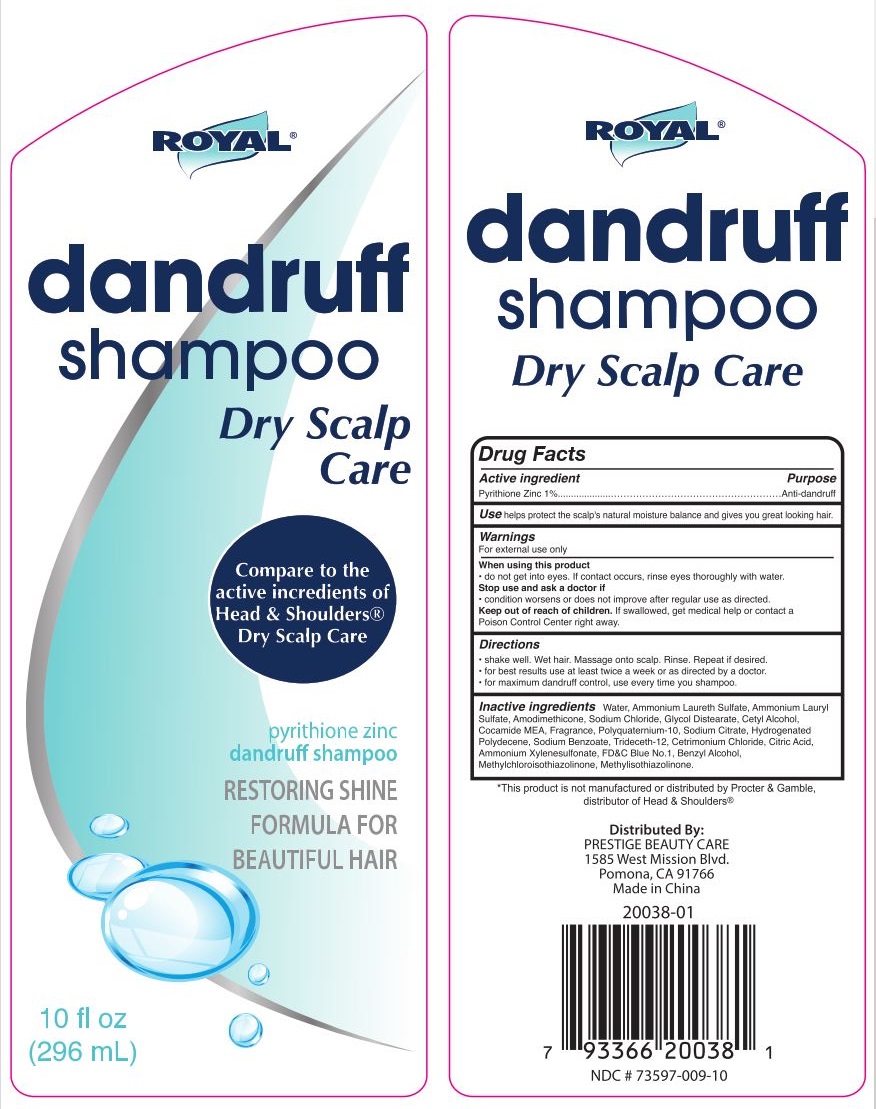 DRUG LABEL: Royal Dandruff Dry Scalp
NDC: 73597-009 | Form: SHAMPOO
Manufacturer: Mission Series Inc. dba Prestige Beauty Care
Category: otc | Type: HUMAN OTC DRUG LABEL
Date: 20200518

ACTIVE INGREDIENTS: PYRITHIONE ZINC 1 g/100 g
INACTIVE INGREDIENTS: AMMONIUM LAURETH-2 SULFATE; AMODIMETHICONE (800 CST); POLYQUATERNIUM-10 (10000 MPA.S AT 2%); SODIUM CITRATE; CITRIC ACID MONOHYDRATE; SODIUM BENZOATE; TRIDECETH-12; FD&C BLUE NO. 1; WATER; BENZYL ALCOHOL; METHYLISOTHIAZOLINONE; AMMONIUM LAURYL SULFATE; HYDROGENATED POLYDECENE TYPE I; SODIUM CHLORIDE; CETYL ALCOHOL; COCO MONOETHANOLAMIDE; CETRIMONIUM CHLORIDE; GLYCOL DISTEARATE; AMMONIUM XYLENESULFONATE; METHYLCHLOROISOTHIAZOLINONE

Royal Dandruff Dry Scalp

Active Ingredient

Active Ingredient - Pyrithione Zinc 1%

Purpose

Anti-dandruff

Use

Use - helps protect the scalp's natural moisture balance and gives you great looking hair.

Warnings

Warnings - For external use only.

When using this product

- do not get into eyes. If contact occurs, rinse eyes thoroughly with water.

Stop Use

Stop use and ask a doctor if

- condition worsens or does not improve after regular use as directed.

Keep out of reach of children. If swallowed, get medical help or contact a Poison Control Center right away.

Directions

- shake well. Wet hair. Massage onto scalp. Rinse. Repeat if desired.

- for best results use at least twice a week or as directed by a doctor.

- for maximum dandruff control, use every time you shampoo.

Inactive Ingredients

Inactive Ingredients - Water, Ammonium Laureth Sulfate, Ammonium Lauryl Sulfate, Amodimethicone, Sodium Chloride, Glycol Distearate, Cetyl Alcohol, Cocamide MEA, Fragrance, Polyquaternium-10, Sodium Citrate, Hydrogentated Polydecene, Sodium Benzoate, Trideceth-12, Cetrimonium Chloride, Citric Acid, Ammonium Xylenesulfonate, FD&C Blue No. 1, Benzyl Alcohol, Methylchloroisothiazolinone, Methylisothiazolinone.

Distributed By

PRESTIGE BEAUTY CARE

1585 West Mission Blvd.

Pomona, CA 91766

Made in China